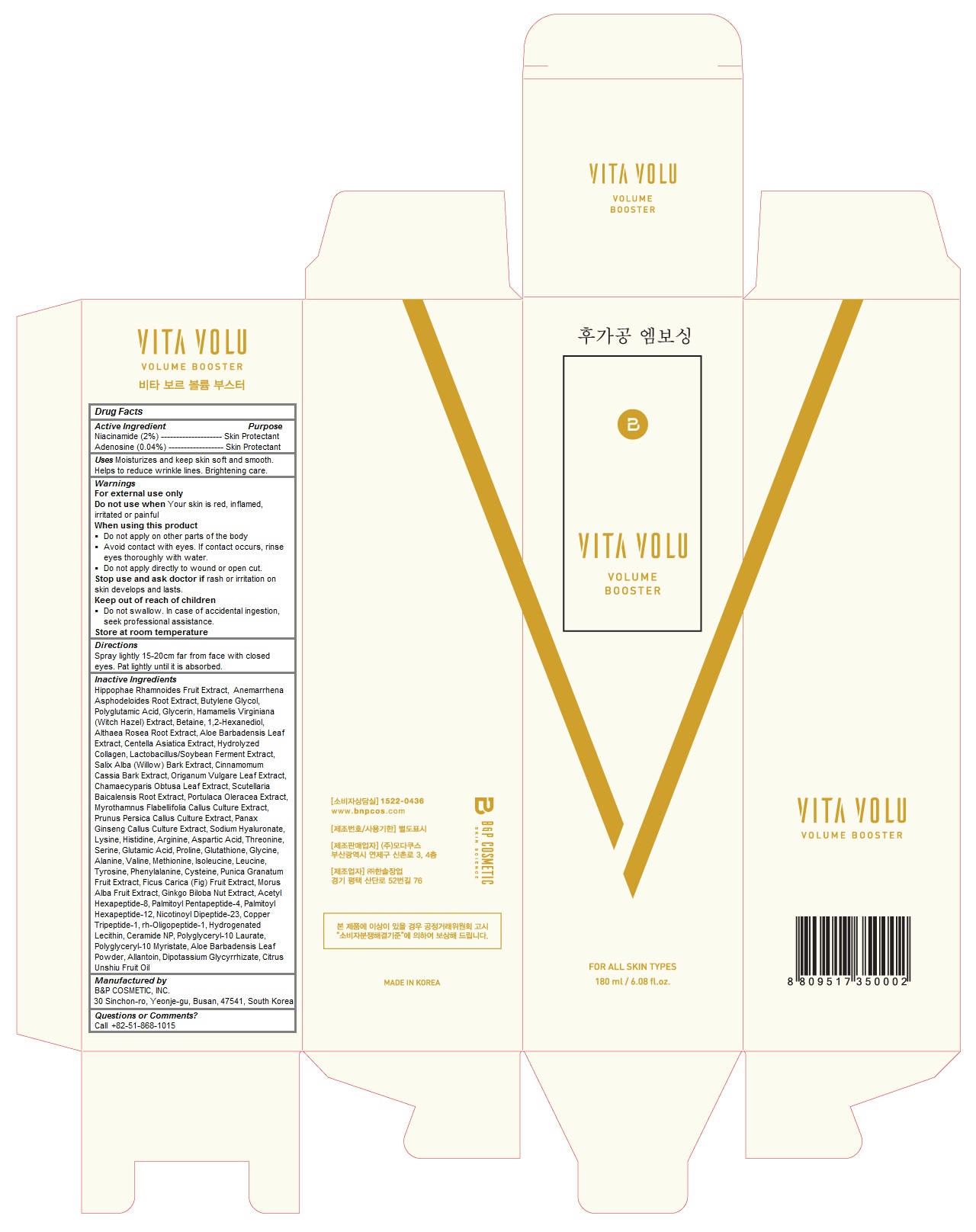 DRUG LABEL: VITA VOLU VOLUME BOOSTER
NDC: 71294-100 | Form: LIQUID
Manufacturer: B&P COSMETIC, INC.
Category: otc | Type: HUMAN OTC DRUG LABEL
Date: 20170303

ACTIVE INGREDIENTS: Niacinamide 3.6 g/180 mL; Adenosine 0.07 g/180 mL
INACTIVE INGREDIENTS: HIPPOPHAE RHAMNOIDES FRUIT; ANEMARRHENA ASPHODELOIDES ROOT; BUTYLENE GLYCOL; Glycerin; HAMAMELIS VIRGINIANA TOP; Betaine; 1,2-Hexanediol; ALCEA ROSEA ROOT; ALOE VERA LEAF; CENTELLA ASIATICA; SALIX ALBA BARK; CHINESE CINNAMON; OREGANO; CHAMAECYPARIS OBTUSA LEAF; SCUTELLARIA BAICALENSIS ROOT; PURSLANE; MYROTHAMNUS FLABELLIFOLIA WHOLE; PEACH; ASIAN GINSENG; HYALURONATE SODIUM; LYSINE; HISTIDINE; Arginine; ASPARTIC ACID; THREONINE; SERINE; GLUTAMIC ACID; Proline; Glutathione; Glycine; Alanine; Valine; Methionine; Isoleucine; Leucine; Tyrosine; Phenylalanine; Cysteine; POMEGRANATE; FIG; WHITE MULBERRY; GINKGO BILOBA SEED; ACETYL HEXAPEPTIDE-8; PALMITOYL PENTAPEPTIDE-4; Palmitoyl Hexapeptide-12; PREZATIDE COPPER; NEPIDERMIN; HYDROGENATED SOYBEAN LECITHIN; Ceramide NP; ALLANTOIN; GLYCYRRHIZINATE DIPOTASSIUM; CITRUS RETICULATA FRUIT OIL

VITA VOLU VOLUME BOOSTER

Active Ingredients

Niacinamide (2%)

Adenosine (0.04%)

Purpose

skin protectant

Keep out of reach of children

- Do not swallow. In case of accidental ingestion, seek professional assistance.

Uses

Moisturizes and keep skin soft and smooth. Helps to reduce wrinkle lines. Brightening care.

Warnings

For external use only
Do not use when Your skin is red, inflamed, irritated or painful
When using this product
 Do not apply on other parts of the body
 Avoid contact with eyes. If contact occurs, rinse eyes thoroughly with water.
 Do not apply directly to wound or open cut.
Stop use and ask doctor if rash or irritation on skin develops and lasts.

Store at room temperature

Directions

Spray lightly 15-20cm far from face with closed eyes. Pat lightly until it is absorbed.

Inactive Ingredients

Hippophae Rhamnoides Fruit Extract, Anemarrhena Asphodeloides Root Extract, Butylene Glycol, Polyglutamic Acid, Glycerin, Hamamelis Virginiana (Witch Hazel) Extract, Betaine, 1,2-Hexanediol, Althaea Rosea Root Extract, Aloe Barbadensis Leaf Extract, Centella Asiatica Extract, Hydrolyzed Collagen, Lactobacillus/Soybean Ferment Extract, Salix Alba (Willow) Bark Extract, Cinnamomum Cassia Bark Extract, Origanum Vulgare Leaf Extract, Chamaecyparis Obtusa Leaf Extract, Scutellaria Baicalensis Root Extract, Portulaca Oleracea Extract, Myrothamnus Flabellifolia Callus Culture Extract, Prunus Persica Callus Culture Extract, Panax Ginseng Callus Culture Extract, Sodium Hyaluronate, Lysine, Histidine, Arginine, Aspartic Acid, Threonine, Serine, Glutamic Acid, Proline, Glutathione, Glycine, Alanine, Valine, Methionine, Isoleucine, Leucine, Tyrosine, Phenylalanine, Cysteine, Punica Granatum Fruit Extract, Ficus Carica (Fig) Fruit Extract, Morus Alba Fruit Extract, Ginkgo Biloba Nut Extract, Acetyl Hexapeptide-8, Palmitoyl Pentapeptide-4, Palmitoyl Hexapeptide-12, Nicotinoyl Dipeptide-23, Copper Tripeptide-1, rh-Oligopeptide-1, Hydrogenated Lecithin, Ceramide NP, Polyglyceryl-10 Laurate, Polyglyceryl-10 Myristate, Aloe Barbadensis Leaf Powder, Allantoin, Dipotassium Glycyrrhizate, Citrus Unshiu Fruit Oil